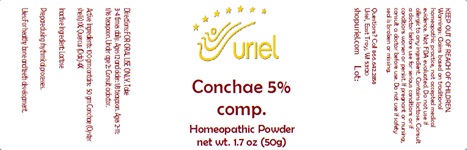 DRUG LABEL: Conchae 5 comp.
NDC: 48951-3116 | Form: POWDER
Manufacturer: Uriel Pharmacy Inc.
Category: homeopathic | Type: HUMAN OTC DRUG LABEL
Date: 20241206

ACTIVE INGREDIENTS: OSTREA EDULIS SHELL 1 [hp_X]/1 g; QUERCUS ROBUR WHOLE 4 [hp_X]/1 g
INACTIVE INGREDIENTS: SUCROSE

Conchae 5 comp.

INDICATIONS AND USAGE

Directions: FOR ORAL USE ONLY

DOSAGE AND ADMINISTRATION

Take 3-4 times daily. Ages 12 and older: 1/8 teaspoon. Ages 2-11: 1/16 teaspoon. Under age 2: Consult a doctor.

Active Ingredients: 100 gm contains:
50 gm Conchae (Oyster shells) 1X; Quercus (Oak) 4X

Inactive Ingredient: Lactose

Prepared using rhythmical processes.

PURPOSE

Uses: For healthy bone and teeth development.

KEEP OUT OF REACH OF CHILDREN.

WARNINGS

Warnings: Claims based on traditional homeopathic practice, not accepted medical evidence. Not FDA evaluated. Do not use if allergic to any ingredient. Contains lactose. Consult a doctor before use for serious conditions or if conditions worsen or persist. If pregnant or nursing, consult a doctor before use. Do not use if safety seal is broken or missing.

QUESTIONS

Questions? Call 866.642.2858 Uriel, East Troy, WI 53120 shopuriel.com Lot: